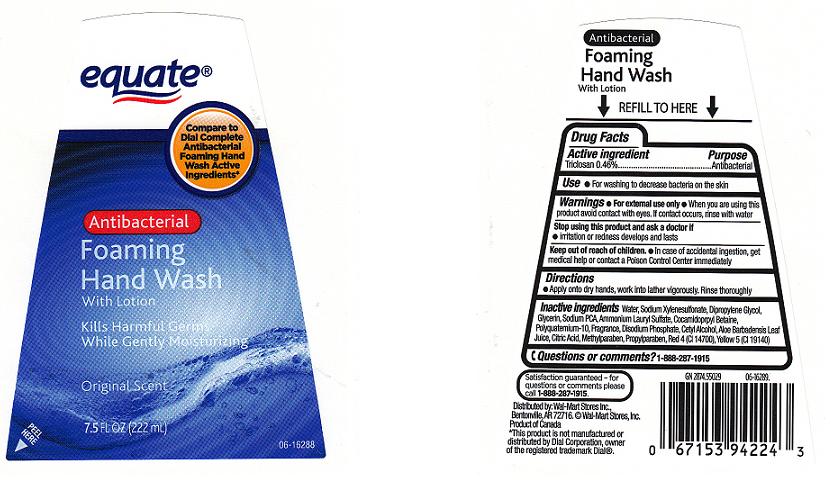 DRUG LABEL: EQUATE
NDC: 49035-177 | Form: SOAP
Manufacturer: WAL-MART STORES INC
Category: otc | Type: HUMAN OTC DRUG LABEL
Date: 20100824

ACTIVE INGREDIENTS: TRICLOSAN 0.4600 mL/100.0000 mL

Drug Facts Box - Back Panel

Active Ingredient

Triclosan 0.46%

Purpose

Antibacterial

Warnings

For external use only.

When using this product

- Avoid contact with eyes. If contact occurs, rinse with water.

Stop using this product and ask doctor if

- Irritation or redness develops and lasts.

Keep out of reach of children

In case of accidental ingestion, get medical help or contact a Poison Control Center immediately.

Uses

For washing to decrease bacteria on the skin.

Directions

Apply onto dry hands, work into a lather vigorously. Rinse thoroughly.

Inactive Ingredients

Water (Aqua), Sodium Xylenesulfonate, Dipropylene Glycol, Glycerin, Sodium PCA, Ammonium Lauryl Sulfate, Cocamidopropyl Betaine, Polyquaternium-10, Fragrance (Parfum), Disodium Phosphate, Cetyl Alcohol, Aloe Barbadensis Leaf Juice, Citric Acid, Methylparaben, Propylparaben, Red 4 (CI 14700), Yellow 5 (CI 19140) .

PACKAGE FRONT AND BACK LABELS

- 7.5 OZ Labels: eq7.5.jpg